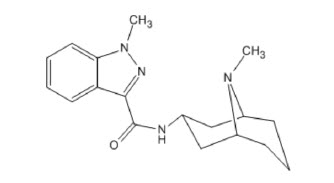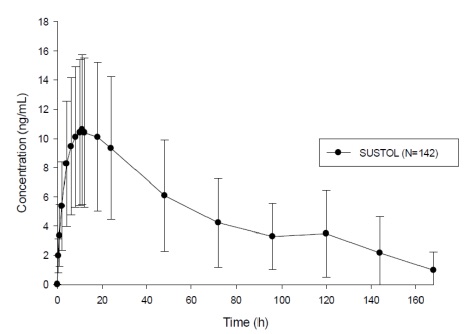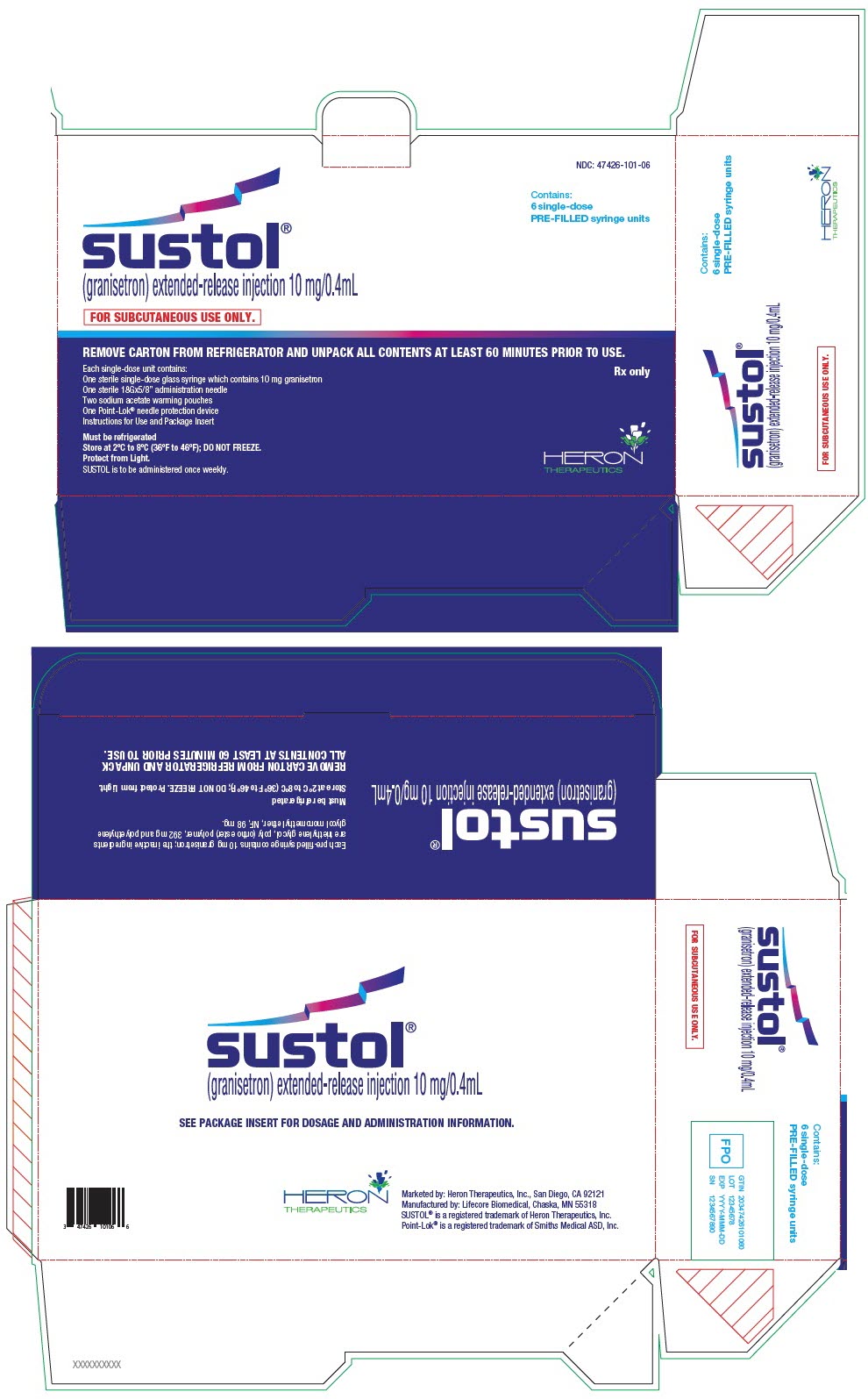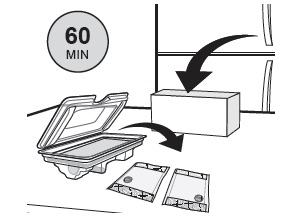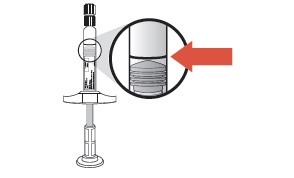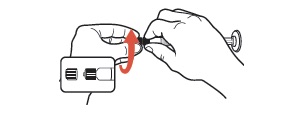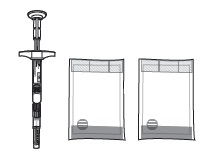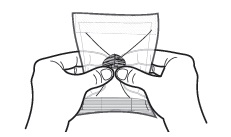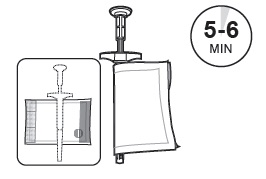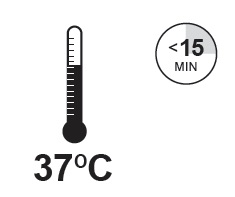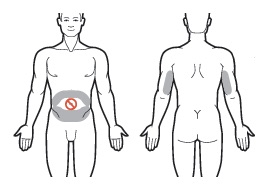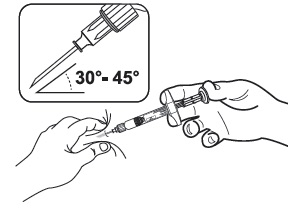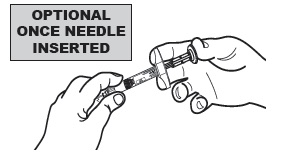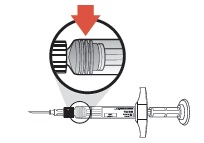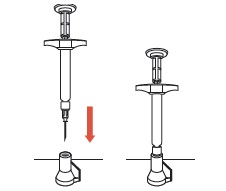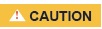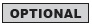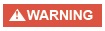 DRUG LABEL: SUSTOL
NDC: 47426-101 | Form: INJECTION
Manufacturer: Heron Therapeutics, Inc.
Category: prescription | Type: HUMAN PRESCRIPTION DRUG LABEL
Date: 20260226

ACTIVE INGREDIENTS: GRANISETRON 10 mg/0.4 mL
INACTIVE INGREDIENTS: POLYETHYLENE GLYCOL MONOMETHYL ETHER 550

HIGHLIGHTS OF PRESCRIBING INFORMATION

These highlights do not include all the information needed to use SUSTOL® safely and effectively. See full prescribing information for SUSTOL.
SUSTOL® (granisetron) extended-release injection, for subcutaneous use
Initial U.S. Approval: 1993

RECENT MAJOR CHANGES

Warnings and Precautions Serious Injection Site Reactions (5.1) | 02/2026

1 INDICATIONS AND USAGE

SUSTOL is a serotonin-3 (5-HT3) receptor antagonist indicated in combination with other antiemetics in adults for the prevention of acute and delayed nausea and vomiting associated with initial and repeat courses of moderately emetogenic chemotherapy (MEC) or anthracycline and cyclophosphamide (AC) combination chemotherapy regimens. (1)

2 DOSAGE AND ADMINISTRATION

Administration (2.1):

- For subcutaneous injection only.
- Intended for administration by a healthcare provider.
- Administer in skin of the back of the upper arm or in the skin of the abdomen at least 1 inch away from the umbilicus.
- Do not administer anywhere the skin is burned, hardened, inflamed, swollen, or otherwise compromised.
- Due to the viscosity, administration requires a slow, sustained injection over 20 to 30 seconds.

Recommended Dosage (2.2):

- The recommended dosage in adults is 10 mg administered as a single subcutaneous injection at least 30 minutes before the start of emetogenic chemotherapy on Day 1.
- Do not administer SUSTOL more frequently than once every 7 days.
- See full prescribing information for recommended dosage of concomitant dexamethasone.

Renal Impairment (2.3):

- In patients with moderate renal impairment (Clcr 30-59 mL/min), administer SUSTOL not more frequently than once every 14 days.
- Avoid SUSTOL in patients with severe renal impairment (CLcr < 30 mL/min).

3 DOSAGE FORMS AND STRENGTHS

Extended-Release Injection: 10 mg/0.4 mL in a single-dose, pre-filled syringe. (3)

4 CONTRAINDICATIONS

Hypersensitivity to granisetron, any of the components of SUSTOL, or to any of the other 5-HT3 receptor antagonists. (4, 5.3)

5 WARNINGS AND PRECAUTIONS

- Serious or severe injection site reactions (ISRs): Infection, prolonged bleeding, bruising, hematomas, nodules, pain, and tenderness have been reported. Patients who are neutropenic or receiving antiplatelet agents or anticoagulants may be at greater risk. Monitor for ISRs during treatment with SUSTOL. Inform patients that some ISRs may occur 2 weeks or more after SUSTOL administration. For ongoing ISRs, administer SUSTOL at a site away from the affected area and consider discontinuing SUSTOL for severe or persistent ISRs. (5.1)
- Gastrointestinal disorders: Monitor for constipation and consider optimizing patients' current bowel regimens used for managing preexisting constipation. Also monitor for decreased bowel activity, particularly in patients with risk factors for gastrointestinal obstruction. Instruct patients to seek immediate medical care if signs and symptoms of ileus occur. (5.2)
- Hypersensitivity reactions: Serious reactions have been reported and may occur up to 7 days or longer following SUSTOL administration and may have an extended course. If a reaction occurs, administer appropriate treatment and monitor until signs and symptoms resolve. (5.3)
- Serotonin syndrome: Reported with 5-HT receptor antagonists alone but particularly with concomitant use of serotonergic drugs. If such symptoms occur, discontinue SUSTOL and initiate supportive treatment. If concomitant use of SUSTOL with other serotonergic drugs is clinically warranted, patients should be made aware of a potential increased risk for serotonin syndrome. (5.4, 7.1)

6 ADVERSE REACTIONS

Most common adverse reactions (≥ 3%) are injection site reactions, constipation, fatigue, headache, diarrhea, abdominal pain, insomnia, dyspepsia, dizziness, asthenia, and gastroesophageal reflux. (6.1)

To report SUSPECTED ADVERSE REACTIONS, contact Heron Therapeutics, Inc. at 844-HERON11 (1-844-437-6611) and www.SUSTOL.com or FDA at 1-800-FDA-1088 or www.fda.gov/medwatch

FULL PRESCRIBING INFORMATION

1 INDICATIONS AND USAGE

SUSTOL is indicated in combination with other antiemetics in adults for the prevention of acute and delayed nausea and vomiting associated with initial and repeat courses of moderately emetogenic chemotherapy (MEC) or anthracycline and cyclophosphamide (AC) combination chemotherapy regimens.

2 DOSAGE AND ADMINISTRATION

2.1 Important Administration Instructions

- For subcutaneous injection only.
- SUSTOL is intended for administration by a health care provider.
- SUSTOL is supplied as a refrigerated kit consisting of a single-dose, pre-filled, sterile syringe, a special thin walled 18 Ga 5/8" administration needle, two syringe warming pouches, and a Point Lok® needle protection device. See the SUSTOL Instructions for Use included in the kit for complete administration instructions with illustrations.
- Do not substitute non-kit components for any of the components from the kit for administration.

Preparation

1. At least 60 minutes prior to administration, remove the SUSTOL kit from refrigeration.
2. Unpack the kit to allow the SUSTOL syringe and all other contents to warm to room temperature.
3. Activate one of the syringe warming pouches, and wrap the SUSTOL syringe in the warming pouch for 5 to 6 minutes to warm SUSTOL to body temperature.
4. Prior to administration, inspect the SUSTOL syringe visually for particulate matter and discoloration. Note that the syringe is amber colored glass. SUSTOL should not be administered if particulate matter or discoloration is observed, the tip cap is missing or has been tampered with, or if the Luer fitting is missing or dislodged.

Administration

1. Use standard aseptic technique when performing the injection.
2. Administer SUSTOL as a single subcutaneous injection in the skin of the back of the upper arm or in the skin of the abdomen at least one inch away from the umbilicus. Avoid injecting SUSTOL anywhere the skin is burned, hardened, inflamed, swollen, or otherwise compromised [see Warnings and Precautions (5.1)]. Topical anesthetic may be used at the injection site prior to administration of SUSTOL.
3. Due to the viscosity of SUSTOL, the time required for injection is greater than most medications administered subcutaneously. SUSTOL requires a slow, sustained injection which may take up to 20 to 30 seconds. Pressing the plunger harder will NOT expel SUSTOL faster.

2.2 Recommended Dosage

The recommended dosage of SUSTOL is 10 mg administered subcutaneously. Administer SUSTOL in combination with dexamethasone at least 30 minutes before the initiation of MEC or AC combination chemotherapy. Administer SUSTOL on Day 1 of chemotherapy and not more frequently than once every 7 days because of the extended-release properties of the formulation.

For patients receiving MEC, the recommended dexamethasone dosage is 8 mg intravenously on Day 1. For patients receiving AC combination chemotherapy regimens, the recommended dexamethasone dosage is 20 mg intravenously on Day 1, followed by 8 mg orally, twice a day, on Days 2, 3 and 4.

If SUSTOL is administered with an NK1 receptor antagonist, see the prescribing information of the NK1 receptor antagonist for the recommended dexamethasone dosage.

2.3 Dosage Adjustment in Renal Impairment

In patients with moderate renal impairment (creatinine clearance of 30 to 59 mL/min), administer SUSTOL on Day 1 of chemotherapy and not more frequently than once every 14 days. Avoid SUSTOL in patients with severe renal impairment (creatinine clearance of less than 30 mL/min) [see Use in Specific Populations (8.6)].

3 DOSAGE FORMS AND STRENGTHS

SUSTOL is supplied as a clear, colorless to slightly yellow, viscous liquid and is available as an:

- Extended-Release Injection: 10 mg/0.4 mL in a single-dose pre-filled syringe.

4 CONTRAINDICATIONS

SUSTOL is contraindicated in patients with hypersensitivity to granisetron, any of the components of SUSTOL, or to any of the other 5-HT3 receptor antagonists [see Warnings and Precautions (5.3), Description (11)].

5 WARNINGS AND PRECAUTIONS

5.1 Serious Injection Site Reactions

Serious or severe injection site reactions (ISRs), including infections (e.g., abscess, cellulitis with gangrene), prolonged bleeding, bruising, hematomas, nodules, pain, and tenderness have been reported in clinical trials [see Adverse Reactions (6.1)] and/or postmarketing. Some postmarketing cases required emergent medical attention, hospitalization, surgical debridement, intravenous antibiotics, and/or incision and drainage. Patients who are neutropenic or receiving concomitant anticoagulant and antiplatelet medications may be at greater risk.

Monitor patients for development of ISRs during treatment with SUSTOL. Inform patients that some ISRs may occur up to 2 weeks or more after SUSTOL administration. For ongoing ISRs, administer SUSTOL at a site away from the affected area [see Dosage and Administration (2.1)]. Consider discontinuing SUSTOL for severe or persistent ISRs.

5.2 Gastrointestinal Disorders

Constipation

In clinical trials, 224 of 1131 (20%) of patients treated with SUSTOL 10 mg reported constipation compared to 13% to 15% in the 5-HT3 receptor antagonist control arms. Hospitalization due to constipation or fecal impaction was reported in 5 SUSTOL-treated patients (0.3%). Monitor patients for the development of constipation while receiving treatment with SUSTOL taking into consideration the extended-release properties of the SUSTOL polymer formulation over at least 5 to 7 days, particularly in patients receiving opioid medications. Consider optimizing bowel regimens in patients using SUSTOL.

Progressive Ileus and Gastric Distention

SUSTOL may mask a progressive ileus and/or gastric distention. This should be particularly considered before use of SUSTOL in patients who have had recent abdominal surgery. Monitor for decreased bowel activity, particularly in patients with risk factors for gastrointestinal obstruction.

5.3 Hypersensitivity Reactions

Hypersensitivity reactions, including anaphylaxis, have been reported in granisetron-treated patients who have exhibited hypersensitivity to other 5-HT3 receptor antagonists [see Contraindications (4)]. Avoid SUSTOL in patients who have had hypersensitivity reactions to other 5-HT3 receptor antagonists [see Contraindications (4)].

Due to the extended-release properties of the SUSTOL polymer formulation, exposure to granisetron may continue for 5 to 7 days following administration. Hypersensitivity reactions may occur up to 7 days or longer following SUSTOL administration and may have an extended course. Inform patients of the signs and symptoms of anaphylaxis, and instruct them to seek immediate medical care should signs and symptoms occur. If hypersensitivity reactions occur, administer appropriate treatment and monitor patients until signs and symptoms resolve.

5.4 Serotonin Syndrome

The development of serotonin syndrome has been reported with 5-HT3 receptor antagonists. Most reports have been associated with concomitant use of serotonergic drugs (e.g., selective serotonin reuptake inhibitors (SSRIs), serotonin and norepinephrine reuptake inhibitors (SNRIs), monoamine oxidase inhibitors, mirtazapine, fentanyl, lithium, tramadol, and intravenous methylene blue). Some of the reported cases were fatal. Serotonin syndrome occurring with overdose of another 5-HT3 receptor antagonist alone has also been reported. The majority of reports of serotonin syndrome related to 5-HT3 receptor antagonist use occurred in a post-anesthesia care unit or an infusion center.

Symptoms associated with serotonin syndrome may include the following combination of signs and symptoms: mental status changes (e.g., agitation, hallucinations, delirium, and coma), autonomic instability (e.g., tachycardia, labile blood pressure, dizziness, diaphoresis, flushing, hyperthermia), neuromuscular symptoms (e.g., tremor, rigidity, myoclonus, hyperreflexia, incoordination), seizures, with or without gastrointestinal symptoms (e.g., nausea, vomiting, diarrhea). Patients should be monitored for the emergence of serotonin syndrome, especially with concomitant use of SUSTOL and other serotonergic drugs. If symptoms of serotonin syndrome occur, discontinue SUSTOL and initiate supportive treatment. Patients should be informed of the increased risk of serotonin syndrome, especially if SUSTOL is used concomitantly with other serotonergic drugs [see Drug Interactions (7.1)].

6 ADVERSE REACTIONS

The following clinically significant adverse reactions are described elsewhere in the labeling:

- Serious Injection Site Reactions [see Warnings and Precautions (5.1)]
- Gastrointestinal Disorders [see Warnings and Precautions (5.2)]
- Hypersensitivity Reactions [see Warnings and Precautions (5.3)]
- Serotonin Syndrome [see Warnings and Precautions (5.4)]

6.1 Clinical Trials Experience

Because clinical trials are conducted under widely varying conditions, adverse reaction rates observed in the clinical trials of a drug cannot be directly compared to rates in the clinical trials of another drug and may not reflect the rates observed in practice.

Studies 1 and 2

The safety of a 10 mg subcutaneous dose of SUSTOL was evaluated in two double-blind, randomized, active-controlled studies, in which 210 patients (23%) received MEC and 467 patients (51%) received AC combination chemotherapy (Studies 1 and 2) [see Clinical Studies (14)]. The data described below reflect exposure to a single 10 mg dose of SUSTOL in 924 patients whose mean age was 56 years (range 19 to 91 years); 76% of patients were female; 70% of patients were Caucasian, 16% Asian, 10% Black, and 4% other races. Dexamethasone was co-administered with SUSTOL in Study 1 and Study 2 and an NK1 receptor antagonist was co-administered with SUSTOL in Study 2.

Table 1 lists the most common adverse reactions reported in at least 3% of patients following a single dose of SUSTOL 10 mg in Study 1 and/or Study 2. Overall, injection site reactions (ISRs) were the most common group of adverse reactions in SUSTOL-treated patients. Specific types of ISRs reported by SUSTOL-treated patients are shown in Table 2.

Table 1. Adverse Reactions Occurring in at Least 3% of Patients Treated with SUSTOL 10 mg in Study 1 and/or Study 2
 | Study 1 |  | Study 2
Adverse Reaction | SUSTOL 10 mg subcutaneous (N=468) % | Palonosetron hydrochloride 0.25 mg intravenous (N=463) % | SUSTOL 10 mg subcutaneous (N=456) % | Ondansetron 0.15 mg/kg intravenous (N=459) %
Injection Site Reactions, any [Rates of individual injection site reactions (ISRs) are shown in Table 2] | 37 | 15 [The placebo subcutaneous injection for Study 1 was normal saline and for Study 2 was a SUSTOL-matched control consisting of the SUSTOL polymer vehicle without active drug.] | 62 | See footnote
Constipation | 14 | 11 | 22 | 15
Fatigue | 11 | 10 | 21 | 24
Headache | 9 | 9 | 13 | 19
Diarrhea | 8 | 7 | 9 | 8
Abdominal Pain | 7 | 7 | 7 | 4
Insomnia | 4 | 2 | 5 | 6
Dyspepsia | 3 | 3 | 6 | 7
Dizziness | 3 | 2 | 5 | 5
Asthenia | 4 | 6 | 2 | 2
Gastroesophageal Reflux | 1 | 1 | 5 | 4

Injection Site Reactions (ISRs) in Studies 1 and 2

Injection site reactions occurred in 37% (175/468) in Study 1, Cycle 1 only, and 62% (281/456) in Study 2 of SUSTOL-treated patients. The ISR manifestations included pain, erythema, mass/nodule, swelling/induration, and bleeding. The incidence of individual ISRs is shown in Table 2. Patients may have experienced one or more types of injection site reactions; a total of 213 of 924 patients had three or more.

ISR reporting procedures included both investigator- and patient-reported outcomes in Study 2, while Study 1 used only investigator reporting.

Table 2. Injection Site Adverse Reactions Following a Single 10 mg SUSTOL Dose
Injection Site Reaction | Study 1 Treatment Arm (Subcutaneous Injection) |  | Study 2 [Patient diary was used in Study 2 to collect ISR information daily.] , [The placebo subcutaneous injection for Study 2 was a SUSTOL-matched control consisting of the SUSTOL polymer vehicle without active drug. ISR data for this group are not shown.] SUSTOL (N=456) %
Injection Site Reaction | SUSTOL (N=468) % | Saline Control (N=463) % | Study 2 [Patient diary was used in Study 2 to collect ISR information daily.] , [The placebo subcutaneous injection for Study 2 was a SUSTOL-matched control consisting of the SUSTOL polymer vehicle without active drug. ISR data for this group are not shown.] SUSTOL (N=456) %
Total Subjects with at least 1 ISR | 37 | 15 | 62
Pain | 3 | 1 | 20
Tenderness | 4 | 1 | 27
Bruising/Hematoma | 22 | 10 | 45
Bleeding | 2 | 1 | 4
Erythema/Redness | 11 | 3 | 17
Swelling/Induration | 1 | 0 | 10
Mass/Nodule | 11 | 1 | 18
Infection at injection site | <1 | 0 | 1
Other [Other includes injection site discoloration, vesicles, irritation, lipoma, paresthesia, pruritus, rash, reaction, scab, scar, and warmth.] | 2 | 1 | 1

Less common adverse reactions reported in less than 3% of SUSTOL-treated patients in clinical trials are syncope, elevation of serum transaminase levels, pancreatitis, atrial fibrillation, somnolence, flushing, and hypersensitivity reactions (e.g., anaphylaxis, urticaria).

Injection Site Reactions in the Safety Database

Reactions at the injection site were assessed in 1814 patients with cancer treated with SUSTOL for one or multiple cycles across four studies (dosing-ranging, open-label, and/or active-controlled), including Study 1 and Study 2. Of the 1814 patients with cancer, 1131 patients were treated with the SUSTOL 10 mg dose. Additionally, infections at the injection site were assessed in 412 healthy subjects treated with any dose of SUSTOL across single- or multiple-dose studies.

- Infections: occurred in 7 of 1814 (0.4%) patients with cancer and 1 of 412 (0.2%) healthy subjects in clinical trials. Injection site infections had a median onset of 9 days (range 7 to 16 days) following SUSTOL administration. One patient who was neutropenic at the time of the infection was hospitalized. All patients with infection were treated with antibiotics and had complete resolution.
- Bruising and/or hematomas: occurred in 426 of 1131 (38%) patients treated with SUSTOL 10 mg with a median time to onset of 2 days. Injection site bruising and/or hematomas with a delayed onset (onset 5 or more days following SUSTOL administration) were reported in 175 (15%) patients. Severe bruising or hematoma (e.g., greater than 4 cm bruise or hematoma) occurred in 3% of patients. Patients receiving concomitant anticoagulant and antiplatelet medications were at greater risk for severe injection site bruising and hematomas.
- Bleeding: occurred in 70 of 1814 (4%) patients treated with SUSTOL. One patient required emergency management. Injection site bleeding for longer than 5 days was reported in 23 (1%) patients.
- Pain and tenderness: In a clinical trial that collected information about injection site pain and tenderness from patient diaries, pain with or without tenderness at the injection site was reported by 91 of 456 (20%) patients treated with SUSTOL 10 mg, and an additional 50 of 456 (11%) patients reported tenderness without pain. Pain and/or tenderness severe enough to require taking pain medication, interfere with patient activity level, or cause significant discomfort at rest was reported in 2% of patients. Among all patients who reported pain and/or tenderness with SUSTOL 10 mg, the median duration was 5 days, and pain lasting longer than 7 days occurred in 6% of patients.
- Nodules: occurred in 203 of 1131 (18%) patients treated with SUSTOL 10 mg and persisted for a median of 15 days; 73 patients (6%) had nodules with durations longer than 21 days.

6.2 Postmarketing Experience

The following adverse reactions have been identified during post-approval use of other formulations of granisetron. Because these reactions are reported voluntarily from a population of uncertain size, it is not always possible to reliably estimate their frequency or establish a causal relationship to drug exposure.

System Organ Class | Adverse Reactions
Cardiovascular | bradycardia, chest pain, palpitations, sick sinus syndrome

7 DRUG INTERACTIONS

7.1 Serotonergic Drugs

Serotonin syndrome (including altered mental status, autonomic instability, and neuromuscular symptoms) has been described following the concomitant use of 5-HT3 receptor antagonists and other serotonergic drugs, including selective serotonin reuptake inhibitors (SSRIs) and serotonin and noradrenaline reuptake inhibitors (SNRIs). Monitor for the emergence of serotonin syndrome. If symptoms occur, discontinue SUSTOL and initiate supportive treatment [see Warnings and Precautions (5.4)].

8 USE IN SPECIFIC POPULATIONS

8.1 Pregnancy

Risk Summary

There are no available data on the use of SUSTOL in pregnant women. Limited published data on granisetron use during pregnancy are not sufficient to inform a drug-associated risk. In animal reproduction studies, no adverse developmental effects were observed in pregnant rats and rabbits administered granisetron hydrochloride during organogenesis at intravenous doses up to 61 times and 41 times respectively the maximum recommended human dose (MRHD) of SUSTOL 10 mg/week [see Data].

The estimated background risk of major birth defects and miscarriage for the indicated population is unknown. All pregnancies have a background risk of birth defect, loss, or other adverse outcomes. In the U.S. general population, the estimated background risk of major birth defects and miscarriage in clinically recognized pregnancies is 2 to 4% and 15 to 20%, respectively.

Data

Animal Data

Reproduction studies with granisetron hydrochloride have been performed in pregnant rats following administration during the period of organogenesis at intravenous doses up to 9 mg/kg/day (approximately 61 times the maximum recommended human dose (MRHD) of SUSTOL 10 mg/week, based on body surface area) and oral doses up to 125 mg/kg/day (approximately 851 times the MRHD of SUSTOL 10 mg/week, based on body surface area). Reproduction studies have been performed in pregnant rabbits in which granisetron hydrochloride was administered during the period of organogenesis at intravenous doses up to 3 mg/kg/day (approximately 41 times the MRHD of SUSTOL 10 mg/week, based on body surface area) and at oral doses up to 32 mg/kg/day (approximately 436 times the MRHD of SUSTOL 10 mg/week, based on body surface area). These studies did not reveal any evidence of impaired fertility or harm to the fetus due to granisetron hydrochloride.

Reproduction studies with the polymer vehicle for SUSTOL have been performed in pregnant rats and rabbits following administration of the polymer vehicle during the period of organogenesis at subcutaneous doses up to 0.295 and 1.18 g per day, respectively, (approximately 45 and 36 times, respectively the amount of polymer vehicle present in the maximum recommended /weekly single human dose of SUSTOL, based on body surface area). These studies did not reveal any evidence of impaired fertility or harm to the fetus due to the polymer vehicle. A pre and postnatal development study with the polymer vehicle for SUSTOL in rats showed no evidence of any adverse effects on pre and postnatal development at subcutaneous doses (administered on gestation days 7 through lactation day 20) up to 0.295 g per day (approximately 45 times the amount of polymer vehicle present in the maximum recommended /weekly single human dose of SUSTOL, based on body surface area).

8.2 Lactation

Risk Summary

There are no data on the presence of SUSTOL in human milk, the effects of SUSTOL on the breastfed infant, or the effects of SUSTOL on milk production. The lack of clinical data during lactation precludes a clear determination of the risk of SUSTOL to an infant during lactation; therefore, the developmental and health benefits of breastfeeding should be considered along with the mother's clinical need for SUSTOL and any potential adverse effects on the breastfed infant from SUSTOL or from the underlying maternal condition.

8.4 Pediatric Use

The safety and effectiveness of SUSTOL in pediatric patients under 18 years of age have not been established.

SUSTOL is not recommended for use in pediatric patients less than 12 years of age because the product administration requires a large gauge needle and an extended administration time.

8.5 Geriatric Use

Of the 738 patients administered 10 mg of SUSTOL in the comparator controlled studies, 177 (24%) were 65 and over while 39 (5%) were 75 and over. No overall differences in safety or effectiveness were observed between these patients and younger patients; and other reported clinical experience has not identified differences in responses between the elderly and younger patients, but greater sensitivity of some older individuals cannot be ruled out.

8.6 Renal Impairment

Breakdown products of the polymer vehicle in SUSTOL can be detected in urine of healthy subjects [see Clinical Pharmacology (12.3)]. There are no pharmacokinetic data regarding elimination of the polymer vehicle of SUSTOL in patients with renal impairment and the clinical significance of potential prolonged elimination is not known. Avoid SUSTOL in patients with severe renal impairment. In patients with moderate renal impairment, administer SUSTOL not more frequently than once every 14 days [see Dosage and Administration (2.3)].

10 OVERDOSAGE

There is no specific antidote for granisetron overdosage. In the case of overdosage, symptomatic treatment should be given. Overdosage of up to 38.5 mg of granisetron hydrochloride, as a single intravenous injection, has been reported without symptoms or with only the occurrence of headache.

11 DESCRIPTION

SUSTOL (granisetron) extended-release injection, contains granisetron, a serotonin-3 (5-HT3) receptor antagonist. Granisetron is 1-methyl-N-[(1R,3r,5S)-9-methyl-9-azabicyclo[3.3.1]non-3-yl]-1H-indazole-3-carboxamide with a molecular weight of 312.4. Its empirical formula is C18H24N4O, with the following chemical structure:

Granisetron is a white to off-white crystalline solid that is insoluble in water.

SUSTOL is a sterile, clear, colorless to slightly yellow, viscous liquid supplied in a single-dose, pre-filled syringe. Each syringe contains 10 mg granisetron incorporated in an extended-release polymer formulation; the inactive ingredients are triethylene glycol poly(orthoester) polymer, 392 mg and polyethylene glycol monomethyl ether, NF, 98 mg.

12 CLINICAL PHARMACOLOGY

12.1 Mechanism of Action

Granisetron is a selective 5-hydroxytryptamine3 (5-HT3) receptor antagonist with little or no affinity for other serotonin receptors, including 5-HT1, 5-HT1A, 5-HT1B/C, 5-HT2; for alpha1-, alpha2-, or beta-adrenoreceptors; for dopamine-D2; or for histamine-H1; benzodiazepine; picrotoxin or opioid receptors.

Serotonin receptors of the 5-HT3 type are located peripherally on vagal nerve terminals and centrally in the chemoreceptor trigger zone of the area postrema. During chemotherapy that induces vomiting, mucosal enterochromaffin cells release serotonin, which stimulates 5-HT3 receptors. This evokes vagal afferent discharge, inducing vomiting. Animal studies demonstrate that, in binding to 5-HT3 receptors, granisetron blocks serotonin stimulation and subsequent vomiting after emetogenic stimuli such as cisplatin. In the ferret animal model, a single granisetron injection prevented vomiting due to high-dose cisplatin or arrested vomiting within 5 to 30 seconds.

12.2 Pharmacodynamics

Cardiac Electrophysiology

The effect of SUSTOL on QTc prolongation was evaluated in a double-blind randomized, four-way crossover, placebo and positive (moxifloxacin) controlled study in 51 adult male and female healthy subjects. At 2-fold the recommended dosage of SUSTOL, there was no significant effect on the QTcF interval.

In 142 cancer patients, 24-hour Holter monitoring and 12-lead ECGs were evaluated. QTcF greater than 450 msec were seen in a total of 20 (19%) patients administered SUSTOL and 9 (31%) patients administered intravenous palonosetron hydrochloride. In the SUSTOL group, one patient had a QTcF interval greater than 500 msec and 4 patients had a change from baseline QTcF greater than 60 msec.

12.3 Pharmacokinetics

Absorption

SUSTOL is an extended-release injection formulation of granisetron using a polymer-based drug delivery system. Following a single-dose administration in healthy subjects, granisetron is released from the polymer over an extended period of time and remains detectable in plasma for 7 days post-dose (Figure 1). A mean concentration of 3.5 ng/mL (range 0 to 14 ng/mL) was observed at 5 days post-dose [see Warnings and Precautions (5.3)].

Figure 1. Plasma Concentrations of Granisetron Over 7 Days after a Single Subcutaneous Injection of SUSTOL in Healthy Subjects

The granisetron pharmacokinetic parameters following injection of SUSTOL were similar between the abdomen and upper arm injection sites as shown in Table 3.

Table 3. Granisetron Pharmacokinetic Parameters Following a Single 10 mg Subcutaneous Injection of SUSTOL in Healthy Subjects by Injection Site Location
Parameter [Values shown are mean ± SD, except for Tmax where median [range] are shown.] | Injection Site Location
Parameter [Values shown are mean ± SD, except for Tmax where median [range] are shown.] | Abdomen N=113 | Upper Arm N=113
Cmax (ng/mL) | 9.8 ± 4.8 | 10.8 ± 4.6
Tmax (hours) [range] | 12 [1 to 144] | 11 [1 to 120]
AUCinf, ng.h/mL | 680 ± 362 | 720 ± 366

In patients, peak plasma granisetron concentrations were delayed compared to healthy subjects with a median Tmax of approximately 24 hours.

Distribution

Plasma protein binding of granisetron is approximately 65% and granisetron distributes freely between plasma and red blood cells.

Metabolism

Published data suggests that granisetron is metabolized by CYP1A1 and CYP3A4. Granisetron metabolism involves N-demethylation and aromatic ring oxidation followed by conjugation.

Elimination

Metabolism: Following a single 10 mg subcutaneous injection of SUSTOL, the terminal elimination half-life of granisetron was approximately 24 hours and was comparable between healthy subjects and patients.

Granisetron clearance is predominantly by hepatic metabolism.

Excretion: Approximately 12% of a granisetron dose, following intravenous administration of granisetron hydrochloride, is eliminated unchanged in the urine in 48 hours. The remainder of the dose is excreted as metabolites, 49% in the urine and 34% in the feces.

Specific Populations

Age: Geriatric Population: In a pooled analysis of samples collected from 56 cancer patients in 3 clinical studies, the mean Cmax and mean AUC0-inf for granisetron following subcutaneous administration of a 10 mg dose of SUSTOL was 39% and 76% higher in patients 65 years of age and older than in patients less than 65 years of age. These pharmacokinetic differences are not considered clinically meaningful taking into consideration the small number of patients 65 years of age and older in the analysis (n = 16) and the high inter-patient variability.

Sex: In a pooled analysis of samples collected from 56 cancer patients in 3 clinical studies, the mean Cmax and mean AUC0-inf for granisetron following subcutaneous administration of a 10 mg dose of SUSTOL was 34% and 132% higher in males than in females. These pharmacokinetic differences are not considered meaningful taking into consideration the small number of males in the analysis (n = 13) and the high inter-patient variability.

Renal Impairment: The total clearance of granisetron was similar in patients with severe renal failure compared to patients with normal renal function following a single 40 mcg/kg intravenous dose of granisetron hydrochloride.

Breakdown products of the polymer vehicle in SUSTOL can be detected in urine of healthy subjects [see Clinical Pharmacology (12.3)]. There are no pharmacokinetic data regarding elimination of the polymer vehicle of SUSTOL in patients with renal impairment [see Dosage and Administration (2.3), Use in Specific Populations (8.6)].

Hepatic Impairment: The total clearance of granisetron was approximately 50% lower in patients with hepatic impairment (neoplastic liver disease) compared to patients with normal hepatic function following a single 40 mcg/kg intravenous dose of granisetron hydrochloride. The high inter-subject variability in the pharmacokinetic parameters of granisetron in patients with hepatic impairment limits the interpretation of these findings.

Drug Interaction Studies

Effect of Other Drugs on Granisetron

Granisetron is metabolized by the hepatic cytochrome P-450 drug-metabolizing enzymes CYP1A1 and CYP3A4. Inducers or inhibitors of CYP1A1 and CYP3A4 enzymes may affect the clearance and half-life of granisetron. In in vitro human microsomal studies, ketoconazole inhibited ring oxidation of granisetron. However, the potential for an in vivo pharmacokinetic interaction with ketoconazole is not known.

Phenobarbital: Administration of intravenous granisetron hydrochloride with phenobarbital, an enzyme inducer, resulted in a 25% increase in total plasma clearance of granisetron. The clinical significance of this interaction is not known.

Effect of Granisetron on Other Drugs

Granisetron does not induce or inhibit the cytochrome P-450 drug-metabolizing enzyme system in vitro. In addition, the in vitro activity of the cytochrome P-450 subfamily 3A4, which is involved in the metabolism of some narcotic analgesics, is not modified by granisetron.

Polymer Breakdown Products

In a metabolic fate study conducted in healthy subjects, breakdown products of the triethylene glycol poly(orthoester) polymer vehicle of the SUSTOL formulation including triethylene glycol (TEG), pentaerythritol (PE), and the oxidative metabolite of TEG, triethylene glycol monocarboxylic acid (TEG acid) were detected in urine with incomplete recovery by the end of study period (10 days). Accumulation of these metabolites in plasma was not noted. The recovery of the polymer load was incomplete in this study and could be due to insufficient sampling and assay sensitivity issues preventing detection of additional metabolites [see Dosage and Administration (2.3), Use in Specific Populations (8.6)].

13 NONCLINICAL TOXICOLOGY

13.1 Carcinogenesis, Mutagenesis, Impairment of Fertility

In a 24-month carcinogenicity study of granisetron hydrochloride, rats were treated orally with 1, 5 or 50 mg/kg/day. The 50 mg/kg/day dose was reduced to 25 mg/kg/day during week 59 due to toxicity. For a 60 kg person, the 1, 5, and 25 mg/kg/day doses represent approximately 7, 34 and 169 times, respectively, the maximum recommended human dose (MRHD) (10 mg granisetron/week, approximately 6.2 mg/m^2/week) of SUSTOL 10 mg/week, based on body surface area. There was a statistically significant increase in the incidence of hepatocellular carcinomas and adenomas in male rats treated with 5 mg/kg/day (approximately 34 times the MRHD of SUSTOL 10 mg/week, based on body surface area) and above, and in female rats treated with 25 mg/kg/day (approximately 169 times the MRHD of SUSTOL 10 mg/week, based on body surface area). No increase in liver tumors was observed at a dose of 1 mg/kg/day (approximately 7 times the MRHD of SUSTOL 10 mg/week, based on body surface area) in male rats and 5 mg/kg/day (approximately 34 times the MRHD of SUSTOL 10 mg/week, based on body surface area) in female rats.

A 24-month subcutaneous carcinogenicity study in rats evaluated the carcinogenic potential of the polymer vehicle in SUSTOL. There were no drug-related neoplasms up to 0.295 g/week (approximately 9 to 30 times the amount of polymer vehicle present in the MRHD of SUSTOL 10 mg/week, based on body surface area).

In a 12-month oral toxicity study with granisetron hydrochloride, rats were treated at 100 mg/kg/day (approximately 677 times the MRHD of SUSTOL 10 mg/week, based on body surface area). This dose produced hepatocellular adenomas in male and female rats while no such tumors were found in the control rats. A 24-month mouse carcinogenicity study of granisetron did not show a statistically significant increase in tumor incidence, but the study was not conclusive. Because of the tumor findings in rat studies, SUSTOL should be prescribed only at the dose and for the indication recommended [see Indications and Usage (1), Dosage and Administration (2.2)].

Granisetron hydrochloride was not mutagenic in an in vitro Ames test and mouse lymphoma cell forward mutation assay, and in vivo mouse micronucleus test and in vitro and ex vivo rat hepatocyte unscheduled DNA synthesis (UDS) assays. However, granisetron hydrochloride was positive in a mouse lymphoma assay with metabolic activation and produced a significant increase in UDS in HeLa cells in vitro and a significant increased incidence of cells with polyploidy in an in vitro human lymphocyte chromosomal aberration test.

Neither SUSTOL nor the polymer vehicle for SUSTOL was mutagenic in the Ames test, mouse lymphoma assay, and the in vivo rat bone marrow micronucleus test.

Granisetron hydrochloride at subcutaneous doses up to 6 mg/kg/day (approximately 40 times the MRHD of SUSTOL 10 mg/week, based on body surface area), and oral doses up to 100 mg/kg/day (approximately 677 times the MRHD of SUSTOL 10 mg/week, based on body surface area) was found to have no effect on fertility and reproductive performance of male and female rats.

The polymer vehicle for SUSTOL at subcutaneous doses up to 0.295 g per day (approximately 137 times the amount of polymer vehicle present in the maximum recommended /weekly single human dose of SUSTOL, based on body surface area) was found to have no adverse effect on fertility and reproductive performance of male and female rats.

14 CLINICAL STUDIES

In a randomized, multicenter, double-blind, parallel group study, a single 10 mg subcutaneous dose of SUSTOL was compared to a single 0.25 mg intravenous dose of palonosetron hydrochloride in cancer patients administered moderately emetogenic (MEC) or anthracycline plus cyclophosphamide (AC) combination chemotherapy. SUSTOL or palonosetron hydrochloride was administered 30 minutes prior to chemotherapy on Day 1. Patients also received either 8 or 20 mg intravenous dexamethasone on Day 1 depending on chemotherapy regimen. Patients who received 20 mg of intravenous dexamethasone also received oral dexamethasone 8 mg twice daily on Days 2, 3, and 4.

In this study of 733 patients (371 in the SUSTOL 10 mg arm and 362 in the palonosetron arm), 79% of patients were female and 63% were Caucasian. The mean age was 57 years (range 22 to 91 years), 55% received MEC and 45% received AC combination chemotherapy regimens. The most common MEC regimens were carboplatin/paclitaxel (31%).

The primary endpoints were proportion of patients with complete response (CR) [defined as no emetic episodes (vomiting or retching) and no use of rescue medication] during the acute phase (0 to 24 hours) and the delayed phase (>24 to 120 hours) following the administration of chemotherapy in Cycle 1. The study design allowed for assessment of non-inferiority of SUSTOL to palonosetron hydrochloride in the acute and delayed phase of MEC and of AC combination chemotherapy.

Non-inferiority of SUSTOL to palonosetron hydrochloride was demonstrated in the acute and delayed phases of MEC and of AC combination chemotherapy [Table 4].

Table 4. Number and Percentage of Patients Who Achieved Complete Response with MEC or AC Combination Chemotherapy [Complete response defined as no emetic episodes and no use of rescue medications.]
Moderately Emetogenic Chemotherapy
Complete Response | SUSTOL 10 mg subcutaneous N=200 n (%) | Palonosetron hydrochloride, 0.25 mg intravenous N=206 n (%) | Difference (95% CI [This study was designed to show non-inferiority in the acute phase or delayed phase for patients receiving moderately emetogenic chemotherapy. A lower bound greater than -15% demonstrates non-inferiority between SUSTOL and comparator.]): SUSTOL minus Palonosetron
Acute Phase (0 – 24 hours) | 166 (83) | 183 (89) | -6 (-13, 1)
Delayed Phase (>24 – 120 hours) | 137 (69) | 144 (70) | -1 (-10, 8)
AC Combination Chemotherapy
Complete Response | SUSTOL 10 mg subcutaneous N=171 n (%) | Palonosetron hydrochloride, 0.25 mg intravenous N=156 n (%) | Difference (95% CI [This study was designed to show non-inferiority in the acute phase and superiority in the delayed phase. A lower bound greater than -15% demonstrates non-inferiority between SUSTOL and comparator. Because a lower bound did not exceed 0%, superiority was not demonstrated between SUSTOL and comparator.]): SUSTOL minus Palonosetron
Acute Phase (0 – 24 hours) | 120 (70) | 99 (64) | 6 (-3, 17)
Delayed Phase (>24 – 120 hours) | 85 (50) | 74 (47) | 2 (-9, 13)

16 HOW SUPPLIED/STORAGE AND HANDLING

SUSTOL extended-release injection is supplied in cartons of six kits (NDC 47426-101-06) each kit contains:

- One sterile single-dose amber colored glass syringe which contains 10 mg granisetron/0.4 mL,
- One sterile 18 Ga 5/8" special thin walled administration needle,
- Two sodium acetate syringe warming pouches,
- One Point Lok needle protection device.

Storage

Store SUSTOL in the refrigerator at 2°C to 8°C (36°F to 46°F).

SUSTOL can be placed back in the refrigerator after being kept at room temperature. SUSTOL can remain at room temperature for up to a maximum of 7 days.

Protect from light. Do not freeze.

17 PATIENT COUNSELING INFORMATION

Advise the patient to read the FDA-approved patient labeling (Medication Guide).

Administration

- SUSTOL is intended for subcutaneous injection by a health care provider.

Injection Site Reactions [see Warnings and Precautions (5.1)]

- Inform the patient that ISRs may occur and may include infections, prolonged bleeding, bruising, hematomas, nodules, pain, and tenderness.
- Inform the patient that some ISRs may occur up to 2 weeks or more after SUSTOL administration.
- Instruct the patient to seek immediate medical care for the following ISRs:
  ο signs of infection at the injection site.
  ο injection site bleeding that is severe or lasts for longer than one day.
- Advise the patient to tell their healthcare provider if they experience:
  ο pain or tenderness severe enough to require treatment with pain medication or interfere with daily activity.
  ο bruising and/or hematoma or a persistent nodule at the injection site.

Gastrointestinal

Advise the patient to report new or worsening constipation to their healthcare provider and seek immediate medical care if signs and symptoms of an ileus occur [see Warnings and Precautions (5.2)].

Hypersensitivity reactions

Advise the patient that hypersensitivity reactions may occur up to 7 days or longer following SUSTOL administration. Inform the patient of the signs and symptoms of hypersensitivity reactions, and have them seek immediate medical care should signs and symptoms occur [see Warnings and Precautions (5.1, 5.3)].

Serotonin Syndrome

Advise the patient of the possibility of serotonin syndrome, especially with concomitant use of SUSTOL and another serotonergic agent such as medications to treat depression and migraines. Advise the patient to seek immediate medical attention if the following symptoms occur: changes in mental status, autonomic instability, neuromuscular symptoms with or without gastrointestinal symptoms [see Warnings and Precautions (5.4)].

Manufactured for: Heron Therapeutics, Inc., Cary, NC 27518
Patent: https://www.herontx.com/patents/

SUSTOL® is a registered trademark of Heron Therapeutics, Inc.
Copyright © 2017-2026 Heron Therapeutics, Inc.

All rights reserved.

MEDICATION GUIDE

SUSTOL® (sus' tol)

(granisetron)

extended-release injection, for subcutaneous use

What is the most important information I should know about SUSTOL?

SUSTOL can cause serious side effects, including:

- Serious injection site reactions. Some injection site reactions may be serious or severe and require medical care. Injection site reactions may include infections, prolonged bleeding, bruising, swelling that is caused by blood that collects under the skin (hematoma), small bumps (nodules) at the injection site, pain, and tenderness. Some injection site reactions can happen up to 2 weeks or more after receiving SUSTOL.
  Tell your healthcare provider if you have:
  ο pain or tenderness that you need to take pain medicine for or if you have pain that interferes with your daily activity.
  ο bruising, hematoma, or a nodule at the injection site that does not go away. Your risk of severe bruising and hematomas at the injection site is increased if you take a blood thinner medicine (anticoagulant or antiplatelet medicine).
  Get medical care right away if you have:
  ο signs of an infection at the injection site, including continued redness or warmth, or if you have a fever.
  ο bleeding at the injection site that is severe or lasts for longer than 24 hours.
- Stomach and intestinal problems. Problems having a bowel movement (constipation) that may be serious, can happen up to 7 days after treatment with SUSTOL. These problems may be more likely in people taking opioid pain medicines. SUSTOL can make it harder to identify certain stomach and bowel problems you may have. Tell your healthcare provider if you have constipation or your constipation worsens after you receive SUSTOL. Get medical care right away if you have pain or swelling in your stomach-area (abdomen).
- Serious allergic reactions. Serious allergic reactions have happened in people who receive SUSTOL and who have had allergic reactions to other medicines used to help prevent nausea and vomiting called 5-HT3 receptor antagonists. Serious allergic reactions can happen up to 7 days or longer after treatment. Get emergency medical help right away if you have any signs or symptoms of a serious allergic reaction, including:
  ο hives
  ο breathing trouble
  ο swollen face
  ο chest pain

What is SUSTOL?

- SUSTOL is a prescription medicine called an "antiemetic."
- SUSTOL is used in adults to help prevent the nausea and vomiting that happens right away or later with certain anti-cancer medicines (chemotherapy).

It is not known if SUSTOL is safe and effective in children under 18 years of age.

Who should not receive SUSTOL?

Do not receive SUSTOL if you are allergic to:

- granisetron or any of the ingredients in SUSTOL. See the end of this Medication Guide for a complete list of ingredients in SUSTOL.
- any other 5-HT3 receptor antagonist medicine used to help prevent nausea and vomiting.

What should I tell my healthcare provider before receiving SUSTOL?

Before receiving SUSTOL, tell your healthcare provider about all of your medical conditions, including if you:

- have constipation
- have had recent stomach-area (abdominal) surgery
- have kidney problems
- are pregnant or plan to become pregnant. It is not known if SUSTOL will harm your unborn baby.
- are breastfeeding or plan to breastfeed. It is not known if SUSTOL passes into your breast milk. Talk to your healthcare provider about the best way to feed your baby if you will receive SUSTOL.

Tell your healthcare provider about all the medicines you take, including prescription and over-the-counter medicines, vitamins, and herbal supplements. Using SUSTOL with certain other medicines can cause serious side effects.

Know the medicines you take. Keep a list of them to show your healthcare provider and pharmacist when you get a new medicine.

How will I receive SUSTOL?

- SUSTOL will be given to you by an injection under your skin (subcutaneously) in the back of your upper arm or in your stomach-area (abdomen) on Day 1 of your chemotherapy cycle.
- SUSTOL will be given to you by a healthcare provider.
- SUSTOL is usually given about 30 minutes before you receive your anti-cancer medicine (chemotherapy).
- You should not receive SUSTOL more often than 1 time every 7 days.

What are the possible side effects of SUSTOL?

SUSTOL may cause serious side effects, including:

- See "What is the most important information I should know about SUSTOL?"
- Serotonin Syndrome. A possible life-threatening problem called serotonin syndrome can happen with medicines called 5-HT3 receptor antagonists, including SUSTOL, especially when used with medicines used to treat depression and migraine headaches called serotonin reuptake inhibitors (SSRIs), serotonin and norepinephrine reuptake inhibitors (SNRIs), monoamine oxidase inhibitors (MAOIs), and certain other medicines. Tell your healthcare provider or nurse right away if you have any of the following symptoms of serotonin syndrome:
  ο agitation, seeing things that are not there (hallucinations), confusion, or coma
  ο fast heartbeat or unusual and frequent changes in your blood pressure
  ο dizziness, sweating, flushing, or fever
  ο tremors, stiff muscles, muscle twitching, overactive reflexes, or loss of coordination
  ο seizures
  ο nausea, vomiting, or diarrhea

The most common side effects of SUSTOL include: injection site reactions, constipation, fatigue, headache, diarrhea, stomach-area (abdominal) pain, trouble sleeping or falling asleep, indigestion, dizziness, weakness, and heartburn.

These are not all the possible side effects of SUSTOL. Tell your healthcare provider if you have any side effect that bothers you or does not go away.

Call your doctor for medical advice about side effects.You may report side effects to FDA at 1-800-FDA-1088.

General Information about the safe and effective use of SUSTOL

Medicines are sometimes prescribed for purposes other than those listed in a Medication Guide. Do not use SUSTOL for a condition for which it was not prescribed. Do not give SUSTOL to other people, even if they have the same symptoms that you have. It may harm them.You can ask your healthcare provider or pharmacist for information about SUSTOL that is written for health professionals.

What are the ingredients in SUSTOL?

Active ingredient: granisetron

Inactive ingredients: triethylene glycol poly(orthoester) polymer and polyethylene glycol monomethyl ether

Manufactured for: Heron Therapeutics, Inc., Cary, NC 27518

Patent: https://www.herontx.com/patents/

SUSTOL® is a registered trademark of Heron Therapeutics, Inc.
Copyright © 2017-2026 Heron Therapeutics, Inc.

All rights reserved.

For more information, go to www.SUSTOL.com or call 1-844-437-6611.

This Medication Guide has been approved by the U.S. Food and Drug Administration
Revised: 02/2026

INSTRUCTIONS FOR USE

SUSTOL® (granisetron) extended-release injection 10 mg/0.4 mL Instructions for Use | You must read these complete instructions before you administer SUSTOL for the first time. SUSTOL must be administered by a healthcare provider.
What is SUSTOL? | SUSTOL is a subcutaneous injection that provides long-acting antiemetic medication to patients receiving chemotherapy. SUSTOL contains a highly viscous polymer that provides sustained release of granisetron. SUSTOL is supplied as part of an administration kit.
When should you administer SUSTOL? | Administer SUSTOL at least 30 minutes before chemotherapy on Day 1 of chemotherapy treatment and not more frequently than once every 7 days, because of the extended-release properties of the formulation.
Before you begin to prepare SUSTOL Injection | Read these critical instructions. Do not substitute any of the components from the kit for administration. Check to make sure the SUSTOL kit contains:
Before you begin to prepare SUSTOL Injection | - One sterile single-dose glass syringe which contains 10 mg granisetron - One sterile 18G x 5/8" administration needle - Two sodium acetate warming pouches - One Point-Lok® needle protection device - Instructions for Use, Package Insert and Medication Guide
Bring SUSTOL to room temperature | STEP | To bring SUSTOL to room temperature:
 | 1 | Remove SUSTOL kit from refrigeration. Open carton and remove tray. Open tray and unpack warming pouches. Wait a minimum of 60 minutes prior to use to allow SUSTOL and the warming pouches to warm to room temperature. SUSTOL may be left out at room temperature overnight, and for up to 7 days, before it must be discarded. SUSTOL may be re-refrigerated if not used within the 7 day period. Warming SUSTOL prior to injection decreases the viscosity and makes administration easier. Bringing SUSTOL to room temperature prior to warming with the sodium acetate warming pouch will facilitate warming of SUSTOL to body temperature.
Prepare the syringe | STEP | Follow these steps to prepare SUSTOL for use:
 | 1 | Examine all contents of the package. Do not use if any component is damaged.
 | 2 | Check the expiration date on the syringe. Do not use if the expiration date has passed.
 | 3 | Remove the perforated flag label from the plunger rod.
 | 4 | To ensure that the syringe contains the full dose, check that the gray stopper is close to or below the black line on the syringe barrel label as shown in the illustration. Do NOT expel air bubbles. For a subcutaneous injection, air bubbles in the syringe will not harm the patient.
 | 5 | Unscrew the tip cap from the end of the pre-filled glass syringe. Do NOT use if the tip cap is missing or has been tampered with. Do NOT use if the Luer fitting is missing or dislodged.
 | 6 | Remove the hub cover from the 18G x 5/8" needle supplied with the syringe. Attach the needle to the syringe and seat the needle securely. Do NOT remove the blue needle cover. Do not substitute with any other needle Use ONLY the 18G x 5/8" needle provided with the syringe because of the highly viscous nature of the medication.
Warm SUSTOL to body temperature | STEP | Just prior to administering the injection, follow these steps:
 |  | SUSTOL must be warmed to body temperature immediately prior to injection to reduce viscosity and facilitate administration. SUSTOL is packaged with two warming pouches. The warming pouches use a non- toxic solution of sodium acetate to create an exothermic (warming) reaction. The second warming pouch can be used if SUSTOL is not immediately administered within the 15 minutes provided by the first warming pouch and needs to be re-warmed. Before activating the warming pouch, make sure that the SUSTOL kit was removed from the refrigerator and that the warming pouches were unpacked from the kit at least 60 minutes prior to use to allow SUSTOL and the warming pouches to warm to room temperature.
 | 1 | To activate the warming pouch, locate the metal disc and grasp with thumb and forefingers of both hands. Flex (bend) the disc rapidly until crystals begin to form (fluid will start to turn white). Massage warming pouch for a few seconds to soften and to increase the activation rate.
 | 2 | Wrap the SUSTOL syringe and needle in the syringe warming pouch. Use the outline on the warming pouch label as a placement guide for the syringe and needle. Fold the warming pouch over the syringe and press fastening strips together. Allow SUSTOL to warm for 5 - 6 minutes in the warming pouch. SUSTOL must be warmed to body temperature immediately prior to injection to reduce viscosity and facilitate administration.
 | 3 | Keep the SUSTOL syringe and needle in the warming pouch until you are ready to administer SUSTOL. The warming pouch will keep the SUSTOL syringe at body temperature for 10 - 15 minutes. If more than 15 minutes has elapsed since warming the SUSTOL syringe, then re-warm the syringe using the second warming pouch prior to injecting SUSTOL. Sodium acetate is a non-toxic salt. In case of a puncture to a warming pouch and the spilling of the solution or crystals, clean up with soap and water. In case of eye contact, flush with water for 15 minutes. In case of skin contact, wash with soap and water. Seek medical attention if irritation develops or persists. Used warming pouches may be safely disposed of in the trash.
Select an injection site | STEP | To select an injection site, use these guidelines:
 | 1 | Use the skin of the abdomen at least one inch from the umbilicus or the skin of the back of the upper arms as sites for subcutaneous injections. For SUBCUTANEOUS injection only. Do NOT inject within 1 inch of the umbilicus or anywhere the skin is: • Burned • Hardened • Inflamed • Swollen • Compromised For subsequent injections, use the same general area of the body. However, be sure not to inject in the exact same place. Administer new injections at least 1 inch from the previous site.
Inject SUSTOL | STEP | Follow these steps to inject SUSTOL:
 | 1 | Remove the syringe from the warming pouch. The white finger flange on the syringe provides better control when administering SUSTOL. Do NOT remove white finger flange.
 | 2 | Remove the blue needle cover. Use standard sharps safety techniques to avoid needle sticks.
 | 3 | Use standard aseptic technique when performing the injection. Pinch the skin and underlying subcutaneous tissue with your non-dominant hand to create a "tent." Insert the needle into the subcutaneous tissue at a 30° - 45° angle with your dominant hand. Administer SUSTOL ONLY as a subcutaneous injection. NEVER administer intravenously, intramuscularly or intraperitoneally.
 | 4 | For additional stability, once the needle is inserted into the subcutaneous tissue, release the "tent" and hold the syringe barrel with your non-dominant hand.
 | 5 | Press the plunger using a slow, firm, and steady push until you have delivered the entire dose. Do not use excessive force to inject the material more quickly, as this will only result in greater difficulty with the injection. Due to the high viscosity of SUSTOL, you will experience resistance when injecting SUSTOL. Apply firm and steady pressure to the plunger for about 20-30 seconds. Pressing harder will NOT expel SUSTOL faster. Do NOT advance or reposition the syringe in the subcutaneous tissue during the injection.
 | 6 | Because SUSTOL is highly viscous, before withdrawing the needle, make sure that the medication is completely expelled by checking the position of the stopper at the base of the syringe barrel.
 | 7 | Withdraw the needle. Do not remove the needle from the syringe. Use the enclosed Point-Lok® device to prevent needle sticks. Place the Point-Lok needle protection device, supplied within the SUSTOL kit, on a secured flat surface. Do not hold the Point-Lok device in your hand. Carefully insert the exposed needle into the opening at the top of the Point-Lok device and push down until the needle is fully seated in the Point-Lok device. This action will seal the needle tip and lock the needle firmly into the Point-Lok device. Discard the protected needle and attached syringe using your organization's standard sharps disposal procedures.
 | 8 | Dispense enclosed Medication Guide to each Patient.
Marketed by: Heron Therapeutics, Inc. 4242 Campus Point Court, Suite 200 San Diego, CA 92121 © 2017 Heron Therapeutics, Inc. Revision Date: May 2017 |  | Questions about how to use SUSTOL? Call the support line toll-free at 844-HERON11 (844-437-6611) or visit www.SUSTOL.com LAM-0000363

PRINCIPAL DISPLAY PANEL - 0.4 mL Syringe Kit Carton

NDC: 47426-101-06

sustol®
(granisetron) extended-release injection 10 mg/0.4mL

Contains:
6 single-dose
PRE-FILLED syringe units

FOR SUBCUTANEOUS USE ONLY.

REMOVE CARTON FROM REFRIGERATOR AND UNPACK ALL CONTENTS AT LEAST 60 MINUTES PRIOR TO USE.

Each single-dose unit contains:
One sterile single-dose glass syringe which contains 10 mg granisetron
One sterile 18Gx5/8" administration needle
Two sodium acetate warming pouches
One Point-Lok® needle protection device
Instructions for Use and Package Insert

Must be refrigerated
Store at 2°C to 8°C (36°F to 46°F); DO NOT FREEZE.
Protect from Light.

SUSTOL is to be administered once weekly.

Rx only

HERON
THERAPEUTICS